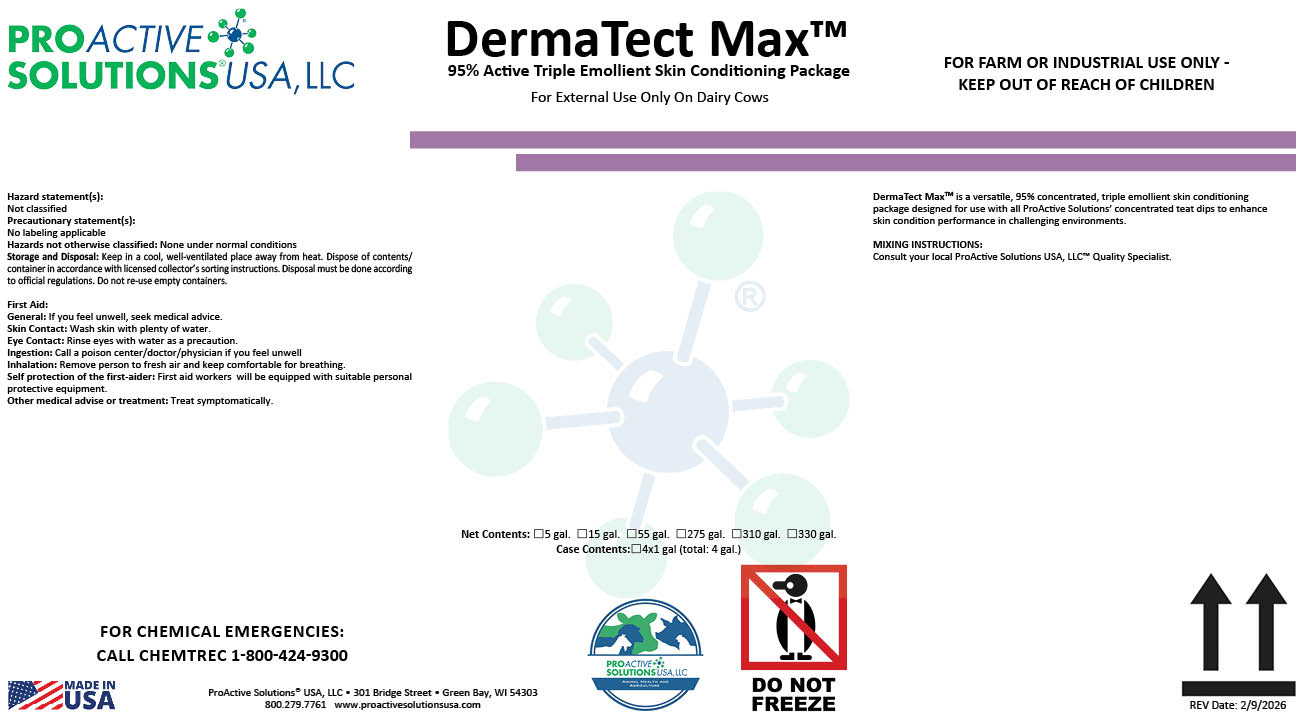 DRUG LABEL: DermaTect Max
NDC: 63927-4143 | Form: SOLUTION
Manufacturer: ProActive Solutions USA LLC
Category: animal | Type: OTC ANIMAL DRUG LABEL
Date: 20260210

ACTIVE INGREDIENTS: GLYCERIN 60.43 kg/100 kg; SORBITOL 11.24 kg/100 kg; PROPYLENE GLYCOL 23.34 kg/100 kg

DermaTect Max

DermaTect Max

DermaTect MaxTM is a versatile, 95% concentrated, triple emollient skin conditioning
package designed for use with all ProActive Solutions’ concentrated teat dips to enhance
skin condition performance in challenging environments.
MIXING INSTRUCTIONS:
Consult your local ProActive Solutions USA, LLC™ Quality Specialist.

Hazard statement(s):
Not classified
Precautionary statement(s):
No labeling applicable
Hazards not otherwise classified: None under normal conditions
Storage and Disposal: Keep in a cool, well-ventilated place away from heat. Dispose of contents/
container in accordance with licensed collector’s sorting instructions. Disposal must be done according
to official regulations. Do not re-use empty containers.
First Aid:
General: If you feel unwell, seek medical advice.
Skin Contact: Wash skin with plenty of water.
Eye Contact: Rinse eyes with water as a precaution.
Ingestion: Call a poison center/doctor/physician if you feel unwell
Inhalation: Remove person to fresh air and keep comfortable for breathing.
Self protection of the first-aider: First aid workers will be equipped with suitable personal
protective equipment.
Other medical advise or treatment: Treat symptomatically.